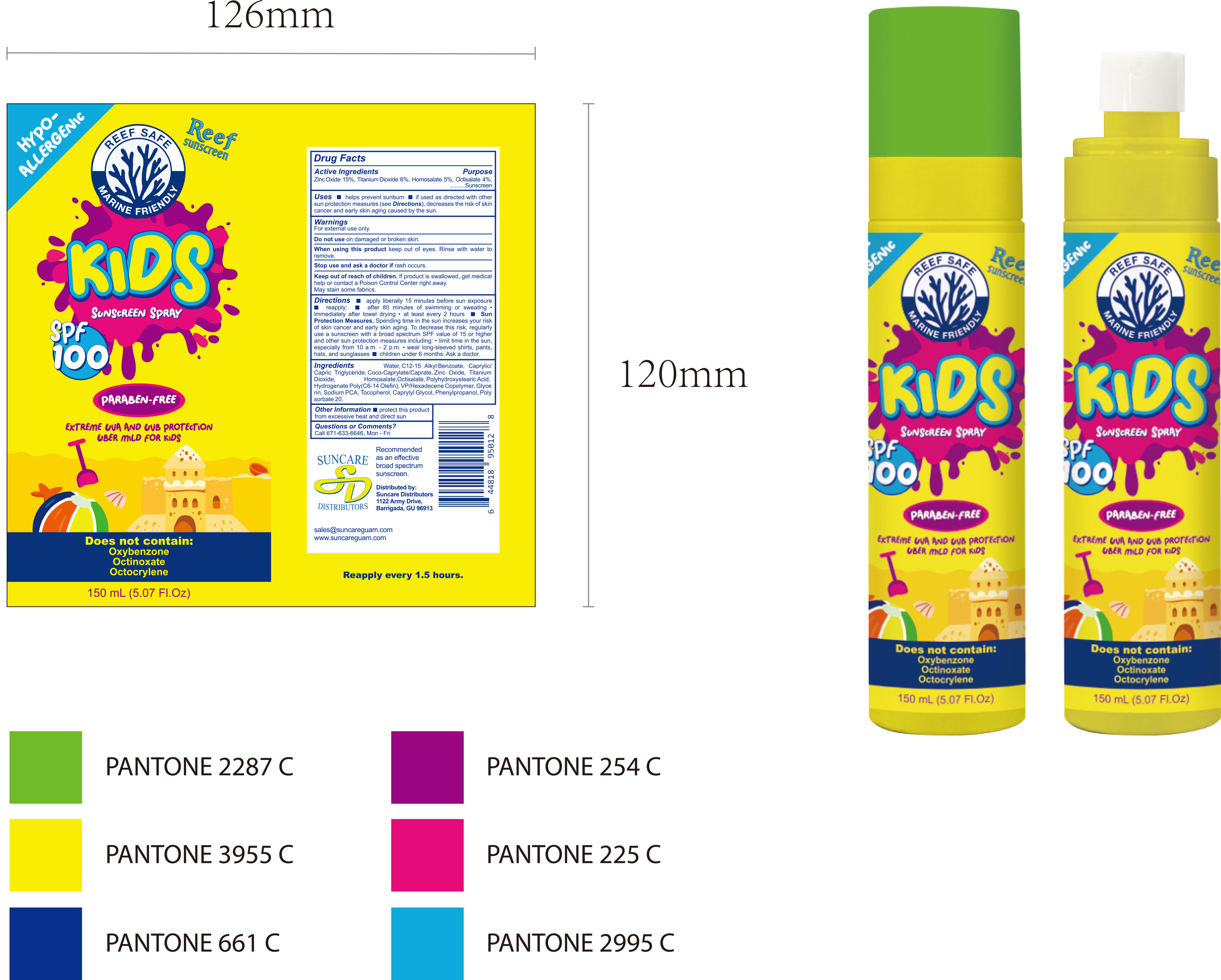 DRUG LABEL: SUNSCREEN SPRAY150ml
NDC: 84938-006 | Form: LIQUID
Manufacturer: Foshan Sugar Max Cosmetics CO.,Ltd
Category: otc | Type: HUMAN OTC DRUG LABEL
Date: 20251216

ACTIVE INGREDIENTS: TITANIUM DIOXIDE 0.06 g/1 mL; ZINC OXIDE 0.15 g/1 mL; HOMOSALATE 0.05 g/1 mL; OCTISALATE 0.04 g/1 mL
INACTIVE INGREDIENTS: POLYHYDROXYSTEARIC ACID (2300 MW); AQUA; HYDROGENATED POLY(C6-14 OLEFIN; 2 CST); C12-15 ALKYL BENZOATE; CAPRYLIC/CAPRIC TRIGLYCERIDE; VP/HEXADECENE COPOLYMER; SODIUM PCA; TOCOPHEROL; CAPRYLYL GLYCOL; PHENYLPROPANOL; POLYSORBATE 20; GLYCERIN; COCO-CAPRYLATE/CAPRATE

84938-006 SUNSCREEN SPRAY

ACTIVE INGREDIENT

Zinc Oxide 15%, Titanium Dioxide 6%, Homosalate 5%, Octisalate 4%

PURPOSE

Sunscreen

INDICATIONS AND USAGE

Uses helps prevent sunburn if used as directed with other sun protection measures (see Directions), decreases the risk of skin cancer and early skin aging caused by the sun.

WARNINGS

For external use only.

Do not use on damaged or broken skin.

When using this product keep out of eyes. Rinse with water to remove.

Stop use and ask a doctor if rash occurs

Keep out of reach of children. lf product is swallowed, get medical help or contact a Poison Control Center right away. May stain some fabrics

DOSAGE AND ADMINISTRATION

Directions apply liberally 15 minutes before sun exposure reapply: after 80 minutes of swimming or sweating Immediately after towel drying "at least every 2 hours Sun Protection Measures. Spending time in the sun increases your risk of skin cancer and early skin aging. To decrease this risk, regularly use a sunscreen with a broad spectrum SPF value of 15 or higher and other sun protection measures including: " limit time in the sun,especially from 10 a.m.-2 p.m.·wear long-sleeved shirts, pants,hats, and sunglasses children under 6 months: Ask a doctor.

INACTIVE INGREDIENT

Aqua (Water)
C12‑15 Alkyl Benzoate
Caprylic/Capric Triglyceride
Coco‑Caprylate/Caprate
Polyhydroxystearic Acid
Hydrogenated Poly(C6‑14 Olefin)
VP/Hexadecene Copolymer
Glycerin
Sodium PCA
Tocopherol
Caprylyl Glycol
Phenylpropanol
Polysorbate 20